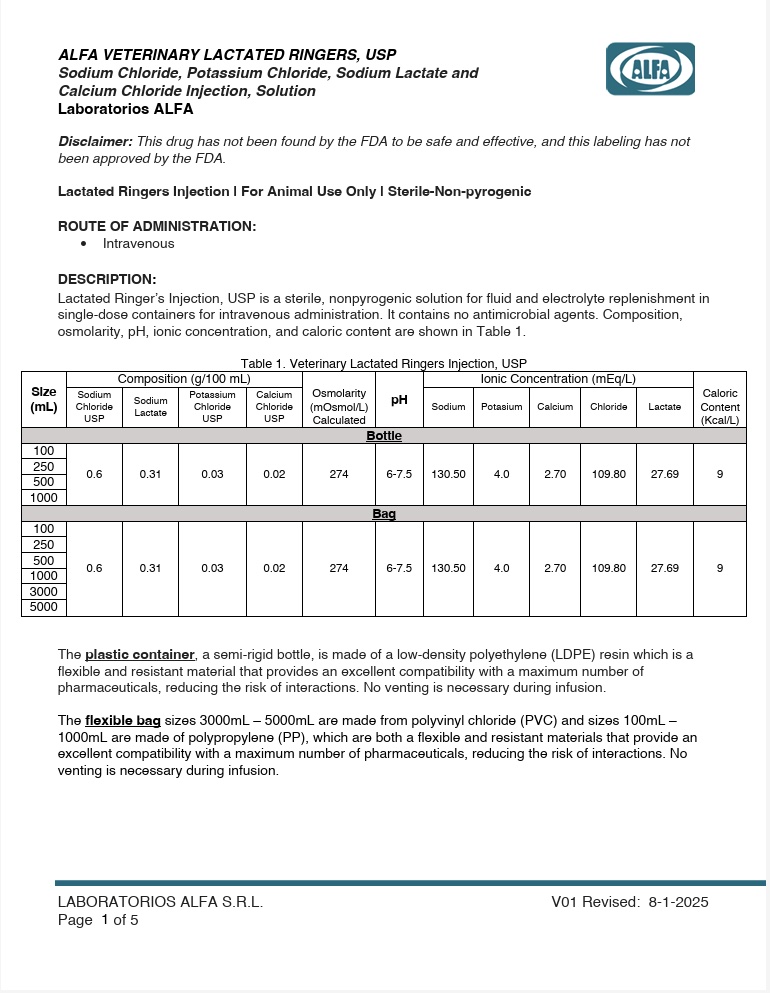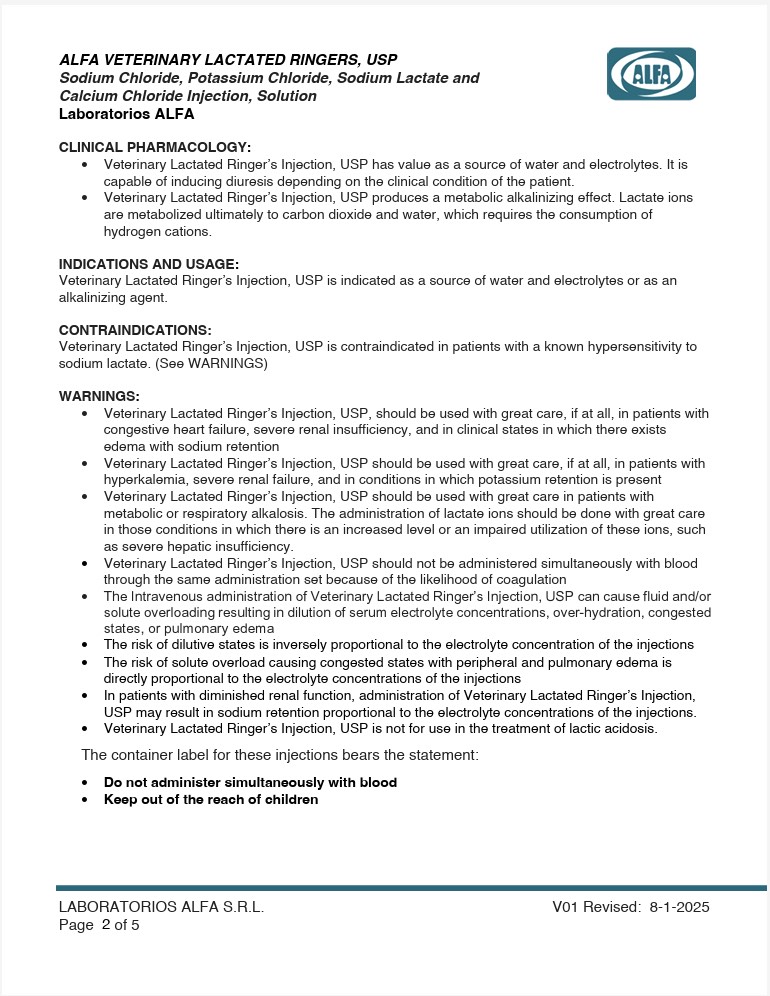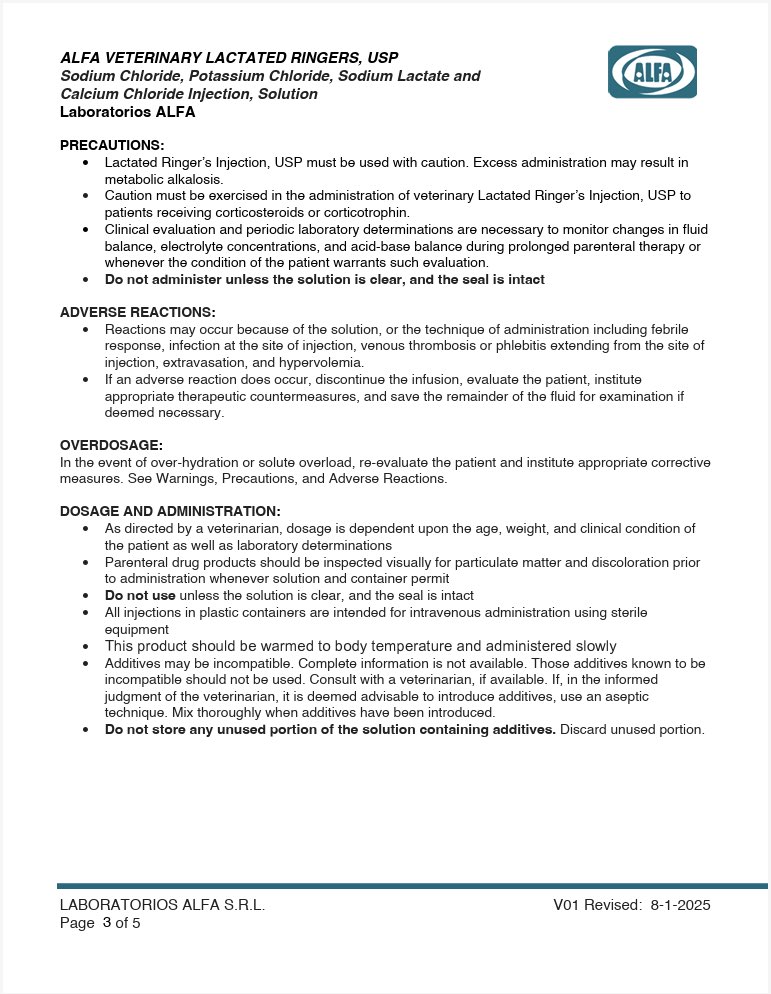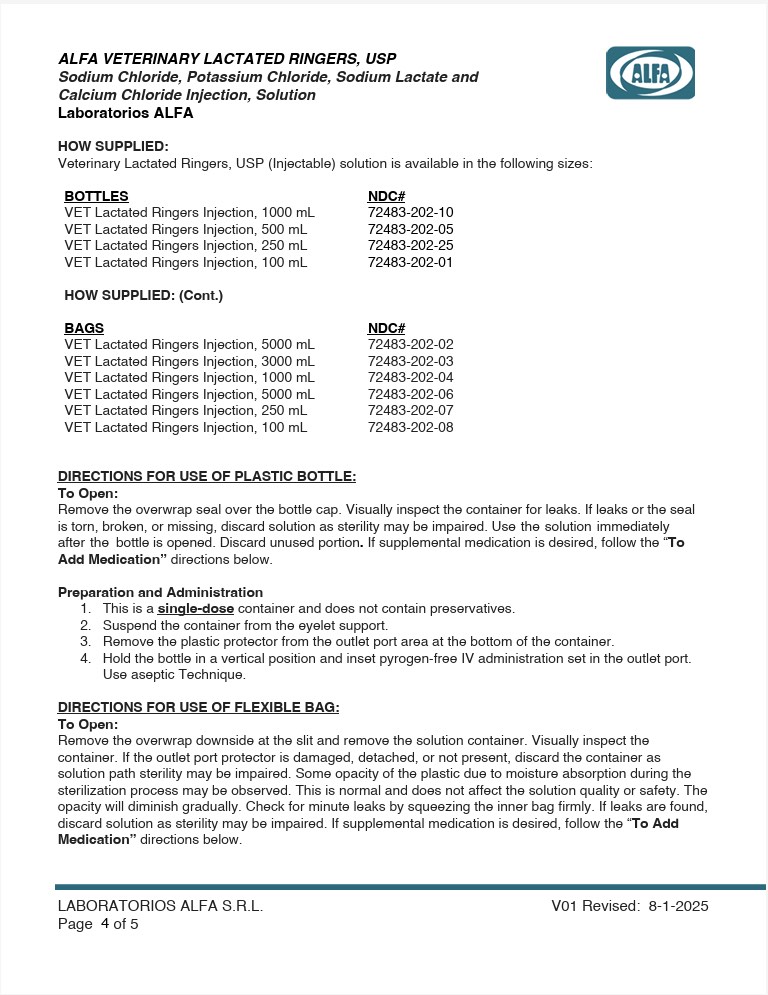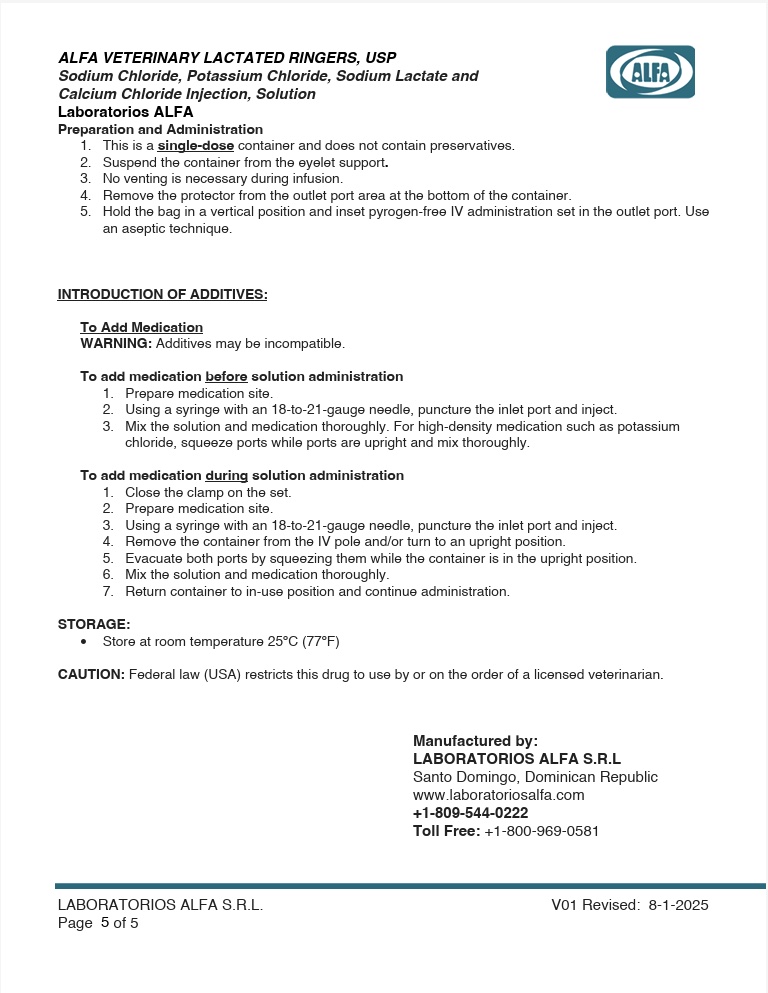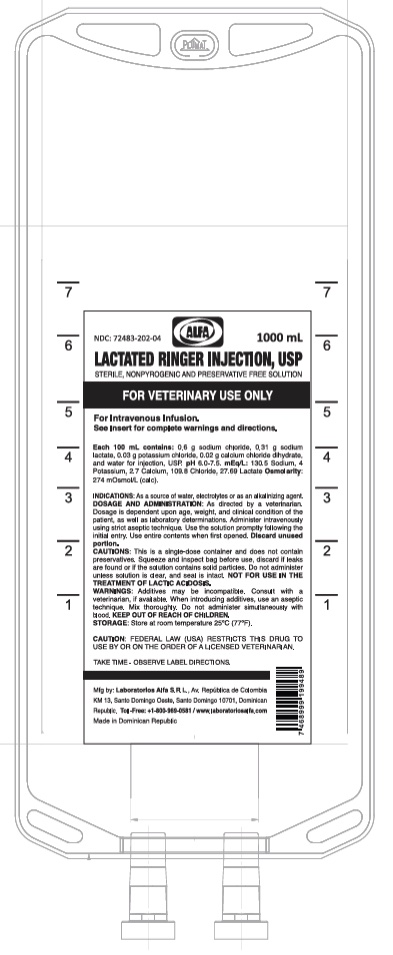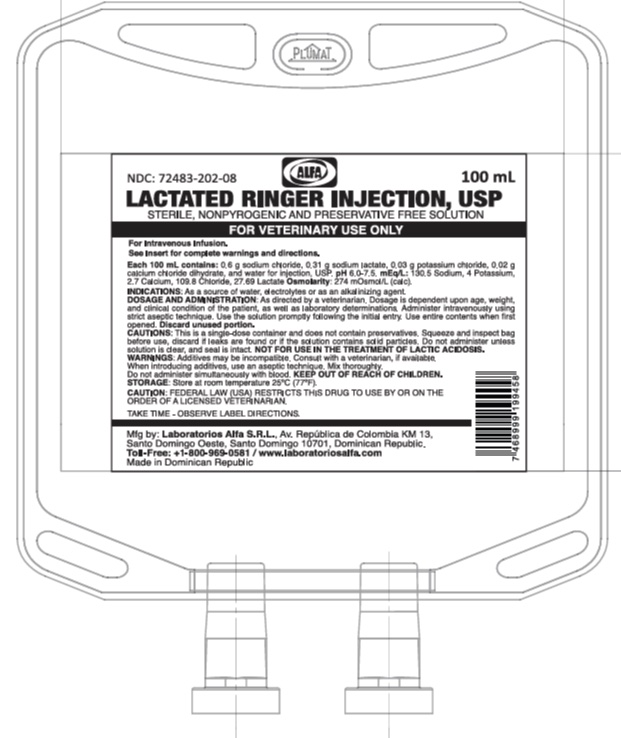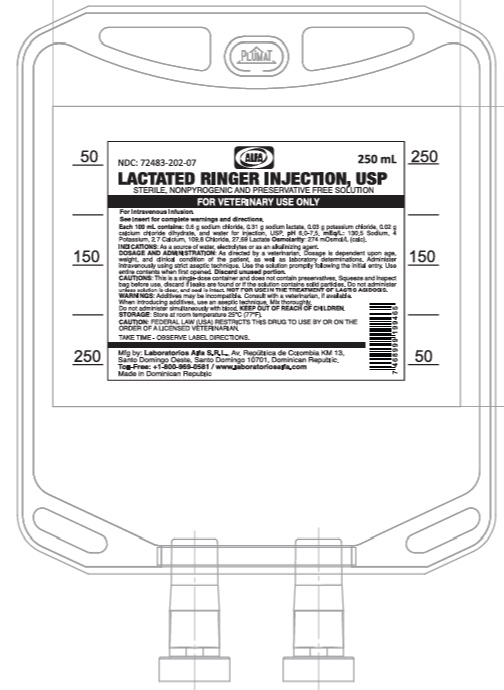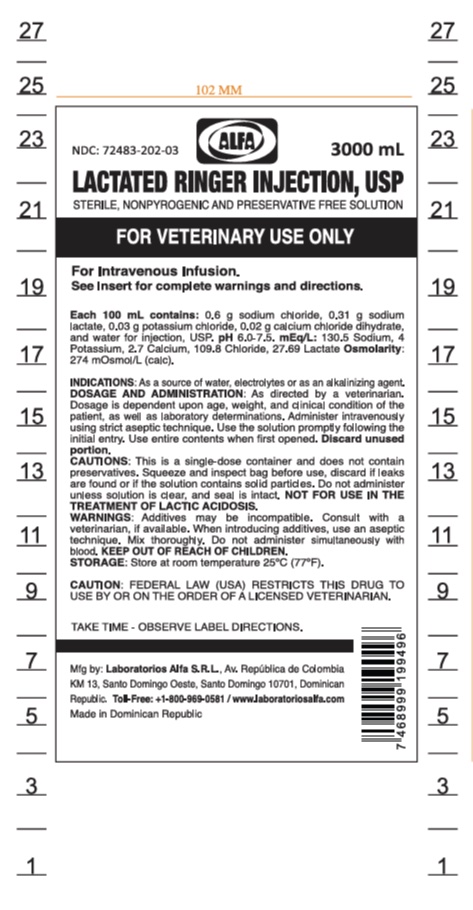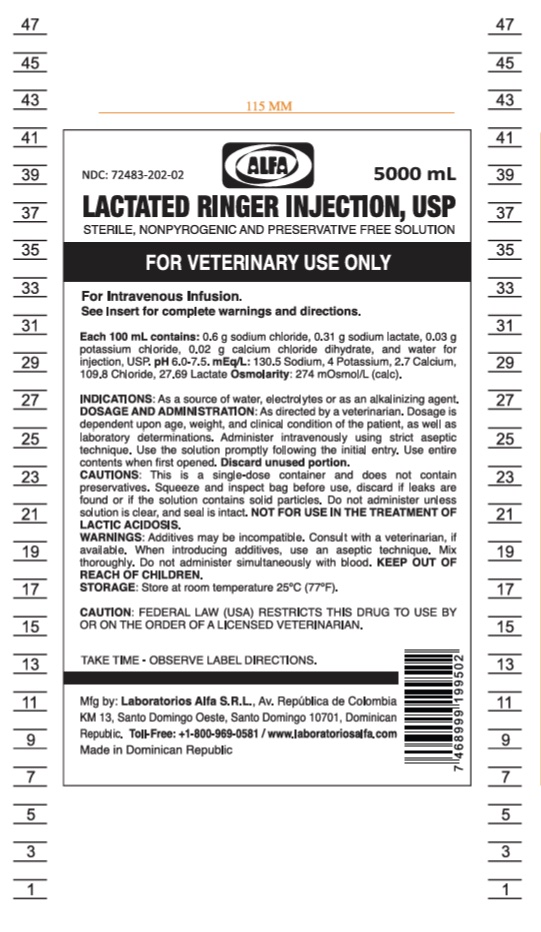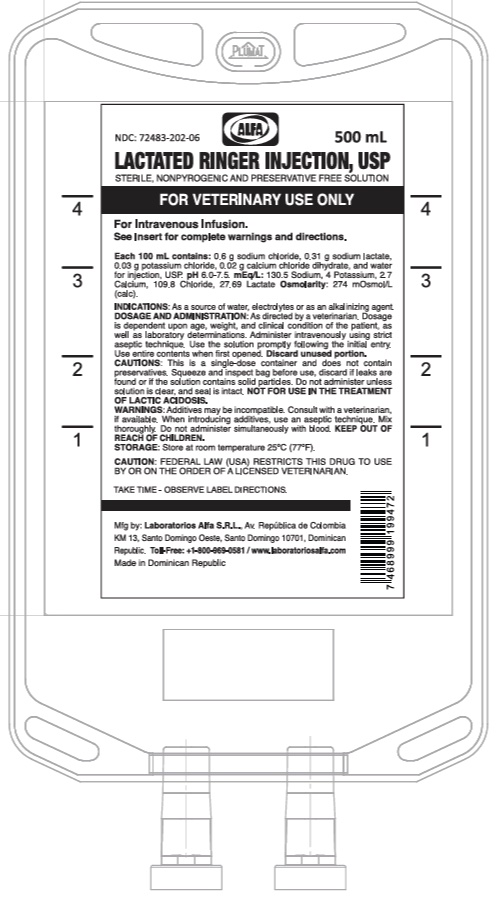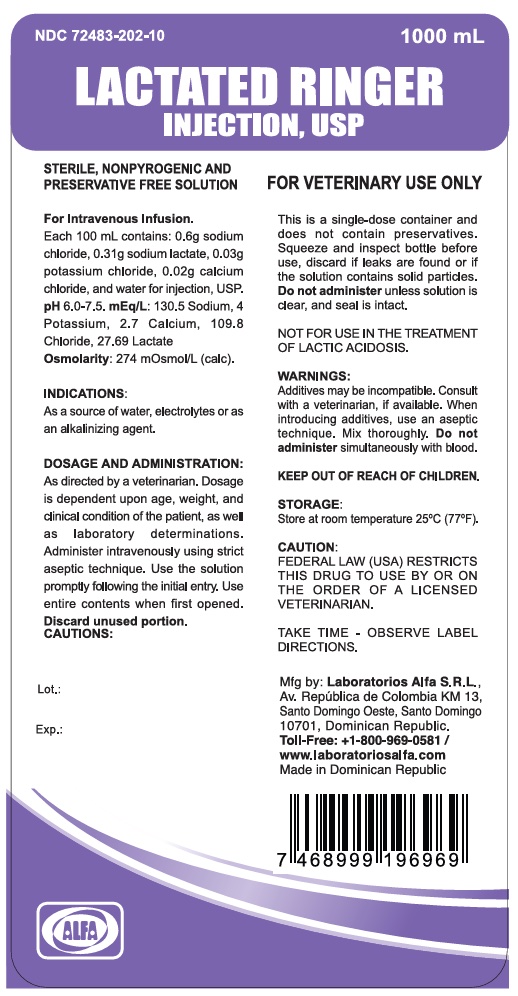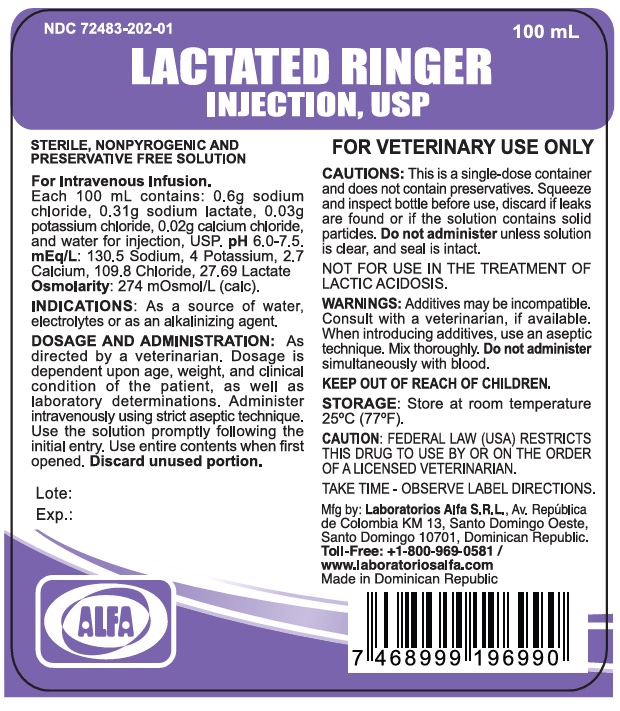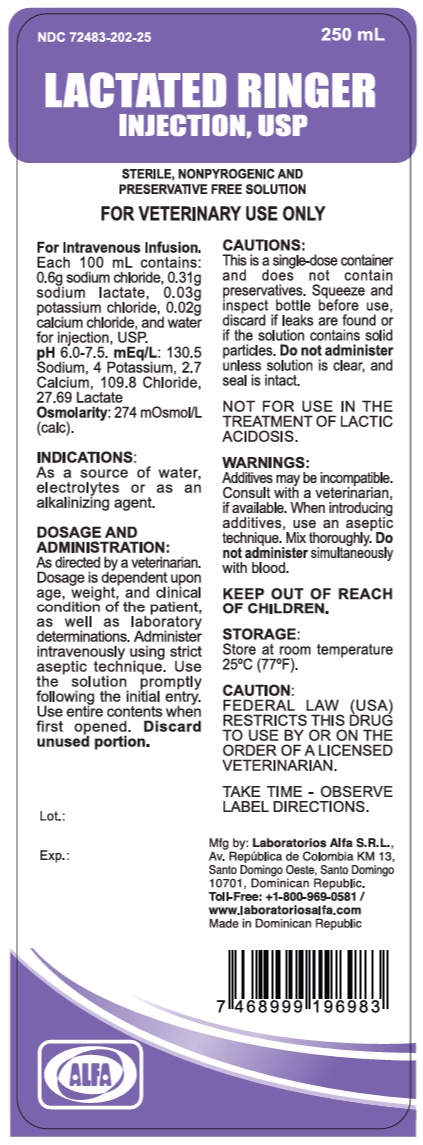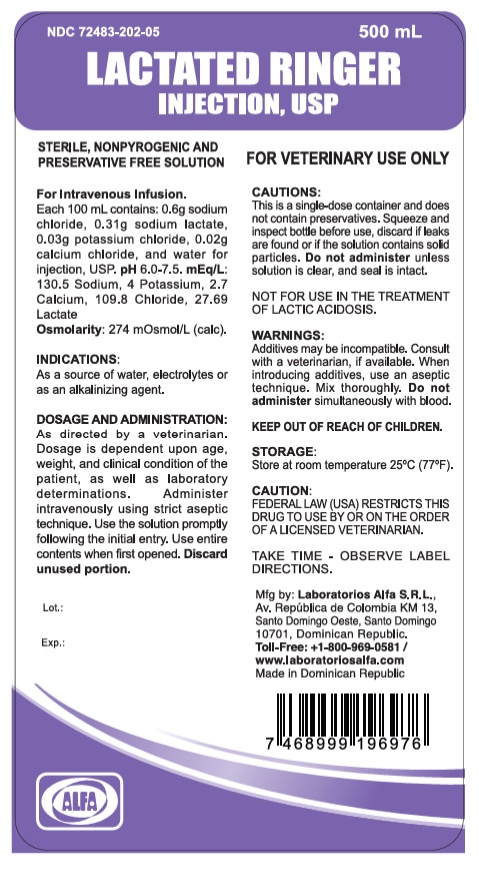 DRUG LABEL: Alfa Veterinary Lactated Ringers
NDC: 72483-202 | Form: INJECTION, SOLUTION
Manufacturer: Laboratorios Alfa SRL
Category: animal | Type: PRESCRIPTION ANIMAL DRUG LABEL
Date: 20250813

ACTIVE INGREDIENTS: SODIUM CHLORIDE 600 mg/100 mL; SODIUM LACTATE 310 mg/100 mL; POTASSIUM CHLORIDE 30 mg/100 mL; CALCIUM CHLORIDE 20 mg/100 mL

DESCRIPTION

Veterinary Lactated Ringers Injection, USP is a sterile, non-pyrogenic solution for fluid replenishment

in single dose containers for intravenous administration. Discard unused portion. It contains no antimicrobial agents.

Table 1.Veterinary Lactated Ringers Injection, USP
Size mL | Composition (g/100 mL) |  |  |  | Osmolarity (mOsmol/L) Calculated | pH | Ionic Concentration (mEq/L) |  |  |  |  | Caloric Content (Kcal/L)
 | Sodium Chloride USP | Sodium Lactate | Potassium Chloride USP | Calcium Chloride USP | Osmolarity (mOsmol/L) Calculated | pH | Sodium | Potasium | Calcium | Chloride | Lactate | Caloric Content (Kcal/L)
100 | 0.6 | 0.31 | 0.03 | 0.02 | 274 | 6-7.5 | 130.50 | 4.0 | 2.70 | 109.80 | 27.69 | 9
250 | 0.6 | 0.31 | 0.03 | 0.02 | 274 | 6-7.5 | 130.50 | 4.0 | 2.70 | 109.80 | 27.69 | 9
500 | 0.6 | 0.31 | 0.03 | 0.02 | 274 | 6-7.5 | 130.50 | 4.0 | 2.70 | 109.80 | 27.69 | 9
1000 | 0.6 | 0.31 | 0.03 | 0.02 | 274 | 6-7.5 | 130.50 | 4.0 | 2.70 | 109.80 | 27.69 | 9

No venting is necessary during infusion.

CLINICAL PHARMACOLOGY

Veterinary Lactated Ringer’s Injection, USP has value as a source of water, electrolytes. It is capable of inducing diuresis depending on the clinical condition of the patient.

Veterinary Lactated Ringer’s Injection, USP produces a metabolic alkalinizing effect. Lactate ions are metabolized ultimately to carbon dioxide and water, which requires the consumption of hydrogen cautions.

INDICATIONS AND USAGE

Veterinary Lactated Ringer’s Injection, USP is indicated as a source of water and electrolytes or as an alkalinizing agent.

CONTRAINDICATIONS

Veterinary Lactated Ringer’s Injection, USP is contraindicated in patients with a known hypersensitivity to sodium lactate.

WARNINGS

Veterinary Lactated Ringer’s Injection, USP, should be used with great care, if at all, in patients with congestive heart failure, severe renal insufficiency, and in clinical states in which there exists edema with sodium retention.

Veterinary Lactated Ringer’s Injection, USP should be used with great care, if at all, in patients with hyperkalemia, severe renal failure, and in conditions in which potassium retention is present.

Veterinary Lactated Ringer’s Injection, USP should be used with great care in patients with metabolic or respiratory alkalosis. The administration of lactate ions should be done with great care in those conditions in which there is an increased level or an impaired utilization of these ions, such as severe hepatic insufficiency.

Veterinary Lactated Ringer’s Injection, USP should not be administered simultaneously with blood through the same administration set because of the likelihood of coagulation.

The container label for these injections bears the statement: Do not administer simultaneously with blood.

The intravenous administration of Veterinary Lactated Ringer’s Injection, USP can cause fluid and/or solute overloading resulting in dilution of serum electrolyte concentrations, over-hydration, congested states, or pulmonary edema.

The risk of dilutive states is inversely proportional to the electrolyte concentration of the injections.

The risk of solute overload causing congested states with peripheral and pulmonary edema is directly proportional to the electrolyte concentrations of the injections.

In patients with diminished renal function, administration of Veterinary Lactated Ringer’s Injection, USP may result in sodium retention proportional to the electrolyte concentrations of the injections.

Veterinary Lactated Ringer’s Injection, USP is not for use in the treatment of lactic acidosis

Keep out of the reach of children.

ADVERSE REACTIONS

Reactions which may occur because of the solution or the technique of administration include febrile response, infection at the site of injection, venous thrombosis or phlebitis extending from the site of injection, extravasation and hypervolemia.

If an adverse reaction does occur, discontinue the infusion, evaluate the patient, institute appropriate therapeutic countermeasures and save the remainder of the fluid for examination if deemed necessary.

PRECAUTIONS

Clinical evaluation and periodic laboratory determinations are necessary to monitor changes in fluid balance, electrolyte concentrations, and acid base balance during prolonged parenteral therapy or whenever the condition of the patient warrants such evaluation.

Lactated Ringer’s Injection, USP must be used with caution. Excess administration may result in metabolic alkalosis.

Caution must be exercised in the administration of veterinary Lactated Ringer’s Injection, USP to patients receiving corticosteroids or corticotrophin.
Reactions which may occur because of the solution or the technique of administration include febrile response, infection at the site of injection, venous thrombosis or phlebitis extending from the site of injection, extravasation, and hypervolemia.
If an adverse reaction does occur, discontinue the infusion, evaluate the patient, institute appropriate therapeutic countermeasures, and save the remainder of the fluid for examination if deemed necessary.

Do not administer unless solution is clear and both seal and container are intact.

DOSAGE AND ADMINISTRATION

As directed by a veterinarian. Dosage is dependent upon the age, weight and clinical condition of the patient, as well as laboratory determinations.

Parenteral drug products should be inspected visually for particulate matter and discolorations prior to administration whenever solution and container permit.

All injections in plastic containers are intended for intravenous administration using sterile equipment.

Additives may be incompatible. Complete information is not available.

Those additives known to be incompatible should not be used.

Consult with pharmacist, if available. If, in the informed judgment of the veterinarian, it is deemed advisable to introduce additives, use aseptic technique. Mix thoroughly when additives have been introduced.

Do not store solutions containing additives. Discard unused portion.

OVERDOSAGE

In an event of over hydration or solute overload, re-evaluate the patient and institute appropriate corrective measures. See Warnings, Precautions and Adverse Reactions.

STORAGE

Store below 30ºC (86ºF).

PRECAUTION OF USE OF THE BOTTLE

This is a single dose container and does not contain preservatives.

Use the solution immediately after the bottle is opened, discard the remaining one.
Squeeze and inspect the bottle, discard if leaks are found or if the solution contains visible and solid particles.

Do not administer simultaneously with blood.
Do not use it unless solution is clear and seal is intact, the solution containing dextrose may be contraindicated in patients with a known allergy to corn or corn products.

DIRECTIONS FOR USE PLASTIC CONTAINER:

Preparation and administration
1. Check for minute leaks by squeezing the container firmly. If leaks are found, discard solution as sterility may be impaired.
2. Suspend container from eyelet support.
3. Remove Plastic protector from ports area at the bottom of container.
4. Hold the bottle in vertical position and inset pyrogen free IV administration set in the outlet port. Use aseptic Technique

To Add Medication
WARNING: Additives may be incompatible.
To add medication before solution administration
1. Prepare medication site.
2. Using syringe with 18 to 21 gauge needle, puncture inlet port and inject.
3. Mix solution and medication thoroughly. For high density medication such as potassium chloride, squeeze ports while ports are upright and mix thoroughly.

To add medication during solution administration
1. Close clamp on the set.
2. Prepare medication site.
3. Using syringe with 18 to 21 gauge needle, puncture inlet port and inject.
4. Remove container from IV pole and/or turn to an upright position.
5. Mix solution and medication thoroughly.
6. Return container to in use position and continue administration.

CAUTION: Federal law (USA) restricts this drug to use by or on the order of a licensed veterinarian.

Package Insert

For animal use only.

PRINCIPAL DISPLAY PANEL (BOTTLES)

LACTATED RINGER’S INJECTION , USP

Veterinary Use

Sterile and NonProgenic Solution

Keep out of reach of Children.

For Animal Use Only.

Take Time - Observe label directions

Manufactured by:

Laboratorios Alfa, SRL

Santo Domingo

Domincan Republic

www.laboratoriosalfa.com

+1-809-544-0222

PRINCIPAL DISPLAY PANEL (BAG)

LACTATED RINGER’S INJECTION , USP

Veterinary Use

Sterile and NonProgenic Solution

Keep out of reach of Children.

For Animal Use Only.

Take Time - Observe label directions

Manufactured by:

Laboratorios Alfa, SRL

Santo Domingo

Domincan Republic

www.laboratoriosalfa.com

+1-809-544-0222